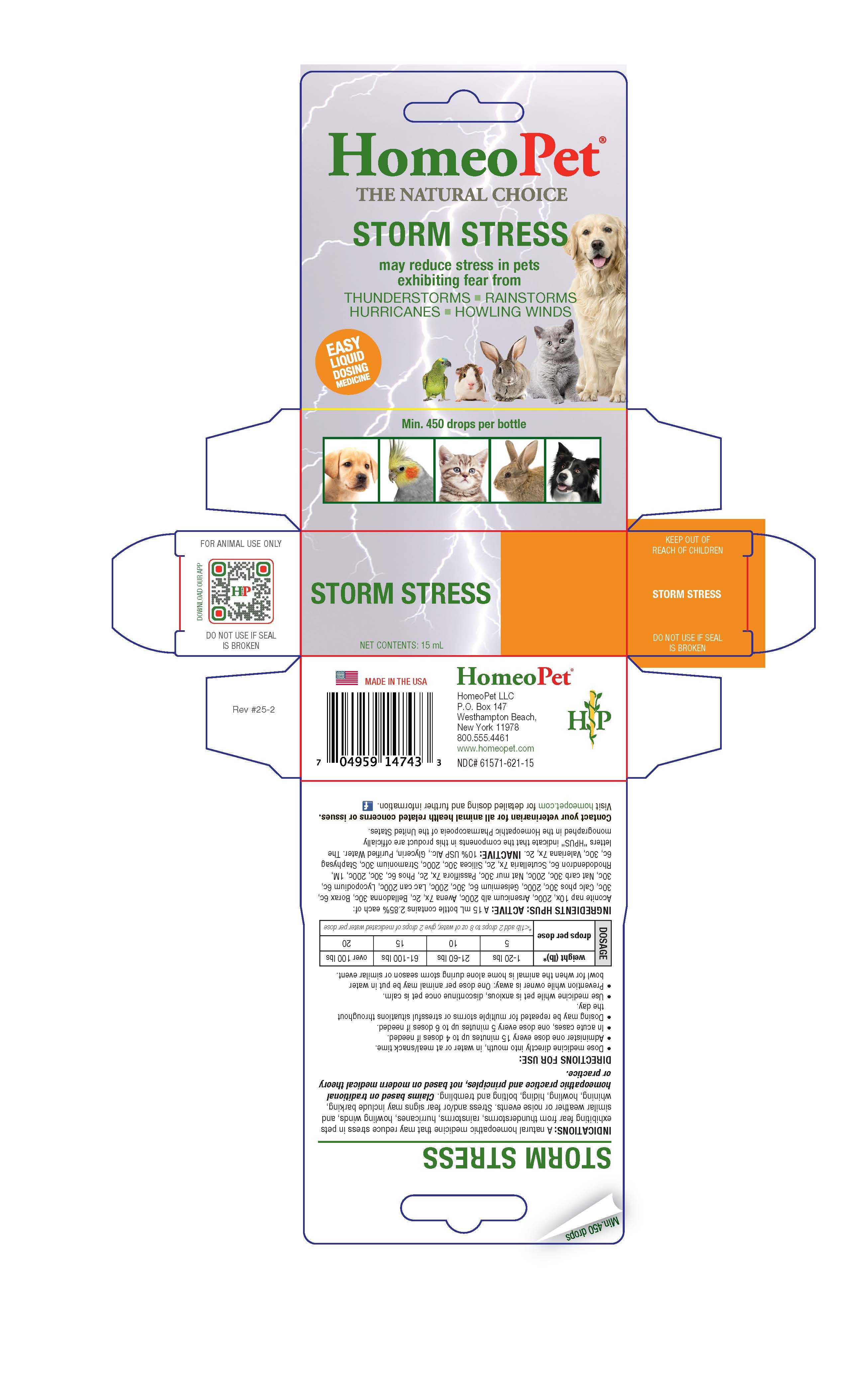 DRUG LABEL: Storm Stress
NDC: 61571-621 | Form: LIQUID
Manufacturer: HomeoPet, LLC
Category: homeopathic | Type: OTC ANIMAL DRUG LABEL
Date: 20251216

ACTIVE INGREDIENTS: ACONITUM NAPELLUS 10 [hp_X]/15 mL; AVENA SATIVA FLOWERING TOP 7 [hp_X]/15 mL; ATROPA BELLADONNA 30 [hp_C]/15 mL; ARSENIC TRIOXIDE 200 [hp_C]/15 mL; SODIUM BORATE 6 [hp_C]/15 mL; TRIBASIC CALCIUM PHOSPHATE 30 [hp_C]/15 mL; GELSEMIUM SEMPERVIRENS ROOT 6 [hp_C]/15 mL; CANIS LUPUS FAMILIARIS MILK 200 [hp_C]/15 mL; LYCOPODIUM CLAVATUM SPORE 6 [hp_C]/15 mL; SODIUM CARBONATE 30 [hp_C]/15 mL; SODIUM CHLORIDE 30 [hp_C]/15 mL; PASSIFLORA INCARNATA TOP 7 [hp_X]/15 mL; PHOSPHORUS 6 [hp_C]/15 mL; RHODODENDRON AUREUM LEAF 6 [hp_C]/15 mL; SCUTELLARIA LATERIFLORA  7 [hp_X]/15 mL; SILICON DIOXIDE 30 [hp_C]/15 mL; DATURA STRAMONIUM 30 [hp_C]/15 mL; DELPHINIUM STAPHISAGRIA SEED 6 [hp_C]/15 mL; VALERIAN 7 [hp_X]/15 mL
INACTIVE INGREDIENTS: ALCOHOL; WATER; GLYCERIN

Storm Stress

Storm Stress

may reduce stress in pets exhibiting fear from

THUNDERSTORMS-RAINSTORMS

HURRICANES-HOWLING WINDS

Directions for Use and Dosage

DIRECTIONS FOR USE:

- Dose remedy directly into mouth, in water or at meal/snack time.
- Administer one dose every 15 minutes up to 4 doses if needed.
- In acute cases, one dose every 5 minutes up to 6 doses if needed.
- Dosing may be repeated for multiple storms or stressful situations throughtout the day.
- Use remedy while pet is anxious, discontinue once pet is calm.
- Prevention while owner is away: One dose per animal may be put in water bowl for when the animal is home alone during storm season or similar event.

DOSAGE
weight (lb)* | drops per dose
1-20 | 5
21-60 | 10
61-100 | 15
over 100 | 20
*<1 lb add 2 drops to 8 oz of wtaer, give 2 drops of medicated water per dose

Contact Veterinarian

Contact Veterinarian if problems persist.

Visit homeopet.com for detailed dosing and further information.

Ingredients HPUS:Active

Aconite nap 10x, 200c, Arsenicum alb 200c, Avena 7x, 2c, Belladonna 30c, Borax 6c, 30c, Calc phos 30c, 200c, Gelsemium 6c, 30c, 200c, Lac can 200c, Lycopodium 6c, 30c, Nat carb 30c, 200c, Nat mur 30c, Passiflora 7x, 2c, Phos 6c, 30c, 200c, 1M, Rhododendron 6c, Scutellaria 7x, 2c, Silicea 30c, 200c, Stramonium 30c, Staphysag 6c, 30c, Valeriana 7x, 2c.

Inactive Ingredients

USP Alcohol, Purified Water

INDICATIONS

A natural homeopathic medicine that may reduce stress in pets exhibiting fear from thunderstorms, rainstorms, hurricanes, howling winds and similar weather or noise events. Stress and/or fear signs may include barking, whining, howling, hiding, bolting and trembling. Claims based on traditional homeopathic practice and principles, not based on modern medical theory or practice.